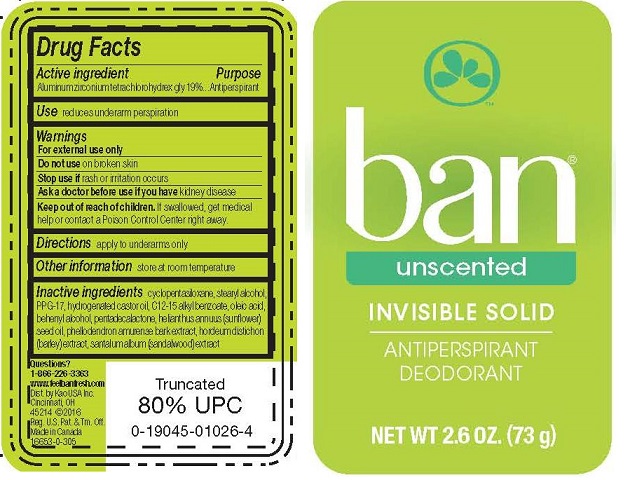 DRUG LABEL: Ban
NDC: 10596-335 | Form: STICK
Manufacturer: Kao USA Inc
Category: otc | Type: HUMAN OTC DRUG LABEL
Date: 20250101

ACTIVE INGREDIENTS: ALUMINUM ZIRCONIUM TETRACHLOROHYDREX GLY 13.87 g/73 g
INACTIVE INGREDIENTS: PPG-17; CYCLOMETHICONE 5; STEARYL ALCOHOL; HYDROGENATED CASTOR OIL; ALKYL (C12-15) BENZOATE; PHELLODENDRON AMURENSE BARK; OLEIC ACID; SANDALWOOD; DOCOSANOL; BARLEY; PENTADECALACTONE; SUNFLOWER OIL

Ban Invisible Solid Antiperspirant Deodorant Unscented

Drug Facts

Active ingredient

Aluminum zirconium tetrachlorohydrex gly 19%

Purpose

Antiperspirant

Use

reduces underarm perspiration

Warnings

For external use only

Do not use on broken skin

Stop use if rash or irritation occurs

Ask a doctor before use if you have kidney disease

Keep out of reach of children. If swallowed, get medical help or contact a Poison Control Center right away.

Directions

apply to underarms only

Other information

store at room temperature

Inactive ingredients

cyclopentasiloxane, stearyl alcohol, PPG-17, hydrogenated castor oil, C12-15 alkyl benzoate, oleic acid, behenhyl alcohol, pentadecalactone, helianthus annus (sunflower) seed oil, phellodendron amurense bark extract, hordeum distichon (barley) extract, santalum album (sandalwood) extract

Questions?

1-866-226-3363

www.feelbanfresh.com

Dist. by Kao USA Inc.

Cincinnati, OH 45214

© 2016 Reg. U.S. Pat. and Tm. Off.

Made in Canada

PACKAGE LABEL

ban®

unscented
INVISIBLE SOLID

ANTIPERSPIRANT DEODORANT

NET WT 2.6 OZ. (73 g)